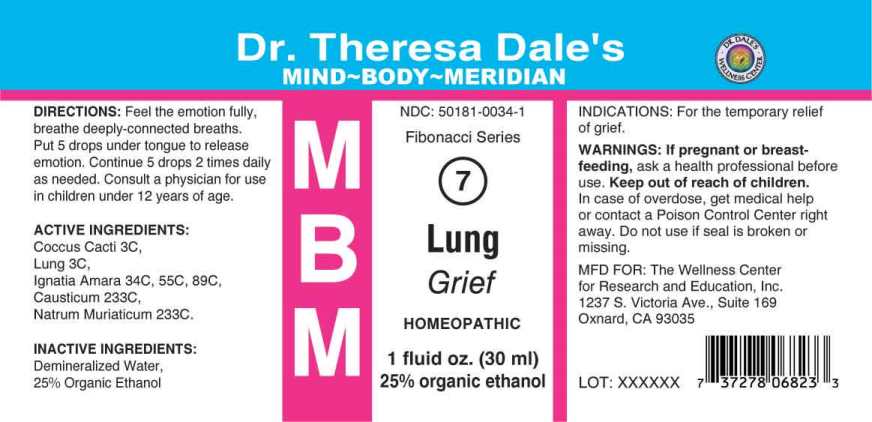 DRUG LABEL: MBM 7 Lung
NDC: 50181-0034 | Form: LIQUID
Manufacturer: The Wellness Center for Research and Education, Inc.
Category: homeopathic | Type: HUMAN OTC DRUG LABEL
Date: 20250604

ACTIVE INGREDIENTS: PROTORTONIA CACTI 3 [hp_C]/1 mL; SUS SCROFA LUNG 3 [hp_C]/1 mL; STRYCHNOS IGNATII SEED 34 [hp_C]/1 mL; CAUSTICUM 233 [hp_C]/1 mL; SODIUM CHLORIDE 233 [hp_C]/1 mL
INACTIVE INGREDIENTS: WATER; ALCOHOL

Drug Facts:

ACTIVE INGREDIENTS:

Coccus Cacti 3C, Lung (Suis) 3C, Ignatia Amara 34C, 55C, 89C, Causticum 233C, Natrum Muriaticum 233C.

INDICATIONS:

For the temporary relief of grief.

WARNINGS:

If pregnant or breast-feeding, ask a health professional before use.

Keep out of reach of children. In case of overdose, get medical help or contact a Poison Control Center right away.

Do not use if seal is broken or missing.

Keep out of reach of children. In case of overdose, get medical help or contact a Poison Control Center right away.

DIRECTIONS:

Feel the emotion fully, breathe deeply-connected breaths. Put 5 drops under tongue to release emotion. Continue 5 drops 2 times daily as needed. Consult a physician for use in children under 12 years of age.

INDICATIONS:

For the temporary relief of grief.

INACTIVE INGREDIENTS:

Demineralized Water, 25% Organic Ethanol

QUESTIONS:

MFD. FOR:

The Wellness Center for Research

and Education, Inc.

1237 S. Victoria Ave. Suite 169

Oxnard, CA 93035

PACKAGE LABEL DISPLAY:

Dr. Theresa Dale's

MIND~BODY~MERIDIAN

NDC: 50181-0034-1

Fibonacci Series

MBM 7

Lung

Grief

HOMEOPATHIC

1 fluid oz. (30ml)